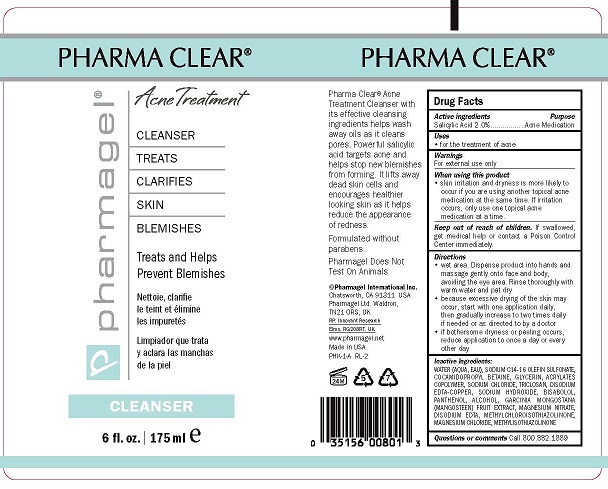 DRUG LABEL: PHARMA CLEAR CLEANSER
NDC: 67879-101 | Form: GEL
Manufacturer: PHARMAGEL INTERNATIONAL INC
Category: otc | Type: HUMAN OTC DRUG LABEL
Date: 20240813

ACTIVE INGREDIENTS: SALICYLIC ACID 2 g/100 mL
INACTIVE INGREDIENTS: WATER; SODIUM C14-16 OLEFIN SULFONATE; CARBOMER COPOLYMER TYPE A; COCAMIDOPROPYL BETAINE; GLYCERIN; CITRIC ACID MONOHYDRATE; DISODIUM EDTA-COPPER; SODIUM HYDROXIDE; TRICLOSAN; PANTHENOL; LEVOMENOL; GARCINIA MANGOSTANA FRUIT; METHYLCHLOROISOTHIAZOLINONE; METHYLISOTHIAZOLINONE

PHARMAGEL - PHARMA CLEAR CLEANSER (67879-101)

ACTIVE INGREDIENTS

Salicylic Acid 2.0%

PURPOSE

Acne Medication

USES:

Use for treatment of acne and to decrease bacteria on the skin.

WARNINGS

For external use only

When using this product:

• avoid contact with the eyes. If product gets into the eyes, rinse thoroughly with water.

• Using other topical acne medications at the same time or immediately following use of this product may increase dryness or irritation of the

skin. If this occurs, only one medication should be used unless directed by a doctor.

• Limit use to the face and neck.

Keep out of reach of children. If swallowed, get medical help or contact a Poison Control Center immediately.

DIRECTIONS:

Wet area. Dispense product into hands and massage gently onto face and body, avoiding the eye area. Rinse thoroughly with warm water and pat dry. For best results, use twice daily.

INACTIVE INGREDIENTS:

WATER (AQUA), SODIUM C14-16 OLEFIN SULFONATE, ACRYLATES COPOLYMER, COCAMIDOPROPYL BETAINE, GLYCERIN, CITRIC ACID, DISODIUM EDTA-COPPER, SODIUM HYDROXIDE, TRICLOSAN, PANTHENOL, BISABOLOL, GARCINIA MANGOSTANA (MANGOSTEEN) FRUIT EXTRACT, METHYLCHLOROISOTHIAZOLINONE, METHYLISOTHIAZOLINONE